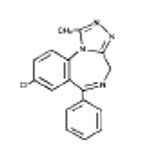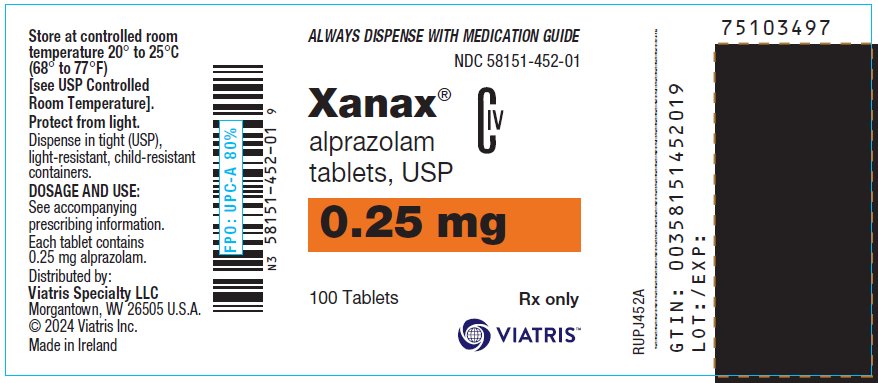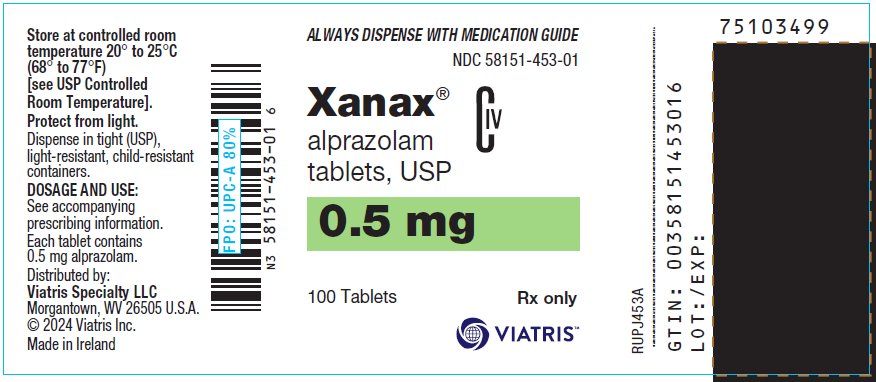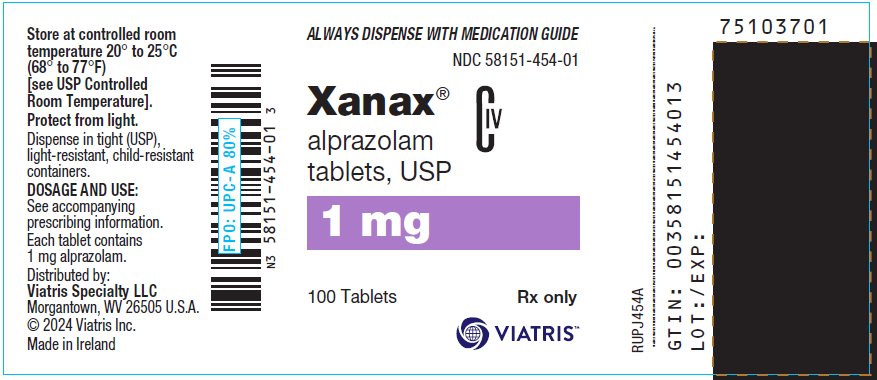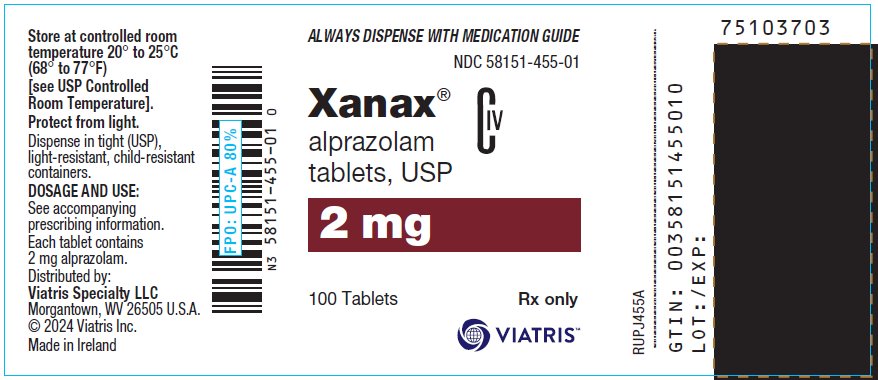 DRUG LABEL: Xanax
NDC: 58151-452 | Form: TABLET
Manufacturer: Viatris Specialty LLC
Category: prescription | Type: HUMAN PRESCRIPTION DRUG LABEL
Date: 20240415
DEA Schedule: CIV

ACTIVE INGREDIENTS: ALPRAZOLAM 0.25 mg/1 1
INACTIVE INGREDIENTS: POWDERED CELLULOSE; STARCH, CORN; DOCUSATE SODIUM; LACTOSE, UNSPECIFIED FORM; MAGNESIUM STEARATE; SILICON DIOXIDE; SODIUM BENZOATE

HIGHLIGHTS OF PRESCRIBING INFORMATION

These highlights do not include all the information needed to use XANAX safely and effectively. See full prescribing information for XANAX.
XANAX (alprazolam) tablets, for oral use, CIV
Initial U.S. Approval: 1981

RECENT MAJOR CHANGES

Warnings and Precautions (5.8) 1/2023

WARNING: RISKS FROM CONCOMITANT USE WITH OPIOIDS; ABUSE, MISUSE, AND ADDICTION; and DEPENDENCE AND WITHDRAWAL REACTIONS

See full prescribing information for complete boxed warning.

- Concomitant use of benzodiazepines and opioids may result in profound sedation, respiratory depression, coma, and death. Reserve concomitant prescribing for use in patients for whom alternative treatment options are inadequate. Limit dosages and durations to the minimum required. Follow patients for signs and symptoms of respiratory depression and sedation. (5.1, 7.1)
- The use of benzodiazepines, including XANAX, exposes users to risks of abuse, misuse, and addiction, which can lead to overdose or death. Before prescribing XANAX and throughout treatment, assess each patient’s risk for abuse, misuse, and addiction. (5.2)
- Abrupt discontinuation or rapid dosage reduction of XANAX after continued use may precipitate acute withdrawal reactions, which can be life-threatening. To reduce the risk of withdrawal reactions, use a gradual taper to discontinue XANAX or reduce the dosage. (2.2, 5.3)

1 INDICATIONS AND USAGE

XANAX is a benzodiazepine indicated for the:

- Acute treatment of generalized anxiety disorder in adults. (1)
- Treatment of panic disorder with or without agoraphobia in adults. (1)

2 DOSAGE AND ADMINISTRATION

- Generalized Anxiety Disorder: (2.1)
  - Recommended starting oral dosage is 0.25 mg to 0.5 mg three times daily.
  - Dosage may be increased, at intervals of every 3 to 4 days, to a maximum recommended daily dose of 4 mg, given in divided doses.
  - Use the lowest possible effective dose and frequently assess the need for continued treatment.
- Panic Disorder: Recommended starting oral dosage is 0.5 mg three times daily. The dosage may be increased at intervals of every 3 to 4 days in increments of no more than 1 mg per day. (2.2)
- When tapering, decrease dosage by no more than 0.5 mg every 3 days. Some patients may require an even slower dosage reduction. (2.3, 5.2)
- See the Full Prescribing Information for the recommended dosage in geriatric patients, patients with hepatic impairment, and with use with ritonavir. (2.4, 2.5, 2.6)

3 DOSAGE FORMS AND STRENGTHS

Tablets: 0.25 mg, 0.5 mg, 1 mg, and 2 mg (3)

4 CONTRAINDICATIONS

- Known hypersensitivity to alprazolam or other benzodiazepines. (4)
- Concomitant use with strong cytochrome P450 3A (CYP3A) inhibitors, except ritonavir. (4, 5.5, 7.1)

5 WARNINGS AND PRECAUTIONS

- Effects on Driving and Operating Machinery: Patients receiving XANAX should be cautioned against operating machinery or driving a motor vehicle, as well as avoiding concomitant use of alcohol and other central nervous system (CNS) depressant drugs. (5.4)
- Patients with Depression: Exercise caution in patients with signs or symptoms of depression. Prescribe the least number of tablets feasible to avoid intentional overdosage. (5.6)
- Neonatal Sedation and Withdrawal Syndrome: XANAX use during pregnancy can result in neonatal sedation and/or neonatal withdrawal. (5.8, 8.1)

6 ADVERSE REACTIONS

The most common adverse reactions reported in clinical trials for generalized anxiety disorder and panic disorder (incidence >5% and at least twice that of placebo) include: impaired coordination, hypotension, dysarthria, and increased libido. (6.1)

To report SUSPECTED ADVERSE REACTIONS, contact Viatris at 1-877-446-3679 (1-877-4-INFO-RX) or FDA at 1-800-FDA-1088 or www.fda.gov/medwatch.

7 DRUG INTERACTIONS

- Use with Opioids: Increase the risk of respiratory depression. (7.1)
- Use with Other CNS Depressants: Produces additive CNS depressant effects. (7.1)
- Use with Digoxin: Increase the risk of digoxin toxicity. (7.1)
- Use with CYP3A Inhibitors (except ritonavir): Increase the risk of adverse reactions of alprazolam. (4, 5.5, 7.1)
- Use with CYP3A Inducers: Increase the risk of reduced efficacy of alprazolam. (7.1)

8 USE IN SPECIFIC POPULATIONS

Lactation: Breastfeeding not recommended. (8.2)

FULL PRESCRIBING INFORMATION

WARNING: RISKS FROM CONCOMITANT USE WITH OPIOIDS; ABUSE, MISUSE, AND ADDICTION; and DEPENDENCE AND WITHDRAWAL REACTIONS

- Concomitant use of benzodiazepines and opioids may result in profound sedation, respiratory depression, coma, and death. Reserve concomitant prescribing of these drugs for patients for whom alternative treatment options are inadequate. Limit dosages and durations to the minimum required. Follow patients for signs and symptoms of respiratory depression and sedation [see Warnings and Precautions (5.1), Drug Interactions (7.1)].
- The use of benzodiazepines, including XANAX, exposes users to risks of abuse, misuse, and addiction, which can lead to overdose or death. Abuse and misuse of benzodiazepines commonly involve concomitant use of other medications, alcohol, and/or illicit substances, which is associated with an increased frequency of serious adverse outcomes. Before prescribing XANAX and throughout treatment, assess each patient’s risk for abuse, misuse, and addiction [see Warnings and Precautions (5.2)].
- The continued use of benzodiazepines, including XANAX, may lead to clinically significant physical dependence. The risks of dependence and withdrawal increase with longer treatment duration and higher daily dose. Abrupt discontinuation or rapid dosage reduction of XANAX after continued use may precipitate acute withdrawal reactions, which can be life‑threatening. To reduce the risk of withdrawal reactions, use a gradual taper to discontinue XANAX or reduce the dosage [see Dosage and Administration (2.2), Warnings and Precautions (5.3)].

1 INDICATIONS AND USAGE

XANAX is indicated for the:

- acute treatment of generalized anxiety disorder (GAD) in adults.
- treatment of panic disorder (PD), with or without agoraphobia in adults.

2 DOSAGE AND ADMINISTRATION

2.1 Dosage in Generalized Anxiety Disorder

The recommended starting oral dosage of XANAX for the acute treatment of patients with GAD is 0.25 mg to 0.5 mg administered three times daily. Depending upon the response, the dosage may be adjusted at intervals of every 3 to 4 days. The maximum recommended dosage is 4 mg daily (in divided doses).

Use the lowest possible effective dose and frequently assess the need for continued treatment [see Warnings and Precautions (5.2)].

2.2 Dosage in Panic Disorder

The recommended starting oral dosage of XANAX for the treatment of PD is 0.5 mg three times daily. Depending on the response, the dosage may be increased at intervals of every 3 to 4 days in increments of no more than 1 mg per day.

Controlled trials of XANAX in the treatment of panic disorder included dosages in the range of 1 mg to 10 mg daily. The mean dosage was approximately 5 mg to 6 mg daily. Occasional patients required as much as 10 mg per day.

For patients receiving doses greater than 4 mg per day, periodic reassessment and consideration of dosage reduction is advised. In a controlled postmarketing dose‑response study, patients treated with doses of XANAX greater than 4 mg per day for 3 months were able to taper to 50% of their total maintenance dose without apparent loss of clinical benefit.

The necessary duration of treatment for PD in patients responding to XANAX is unknown. After a period of extended freedom from panic attacks, a carefully supervised tapered discontinuation may be attempted, but there is evidence that this may often be difficult to accomplish without recurrence of symptoms and/or the manifestation of withdrawal phenomena [see Dosage and Administration (2.3)].

2.3 Discontinuation or Dosage Reduction of XANAX

To reduce the risk of withdrawal reactions, use a gradual taper to discontinue XANAX or reduce the dosage. If a patient develops withdrawal reactions, consider pausing the taper or increasing the dosage to the previous tapered dosage level. Subsequently decrease the dosage more slowly [see Warnings and Precautions (5.3), Drug Abuse and Dependence (9.3)].

Reduced the dosage by no more than 0.5 mg every 3 days. Some patients may benefit from an even more gradual discontinuation. Some patients may prove resistant to all discontinuation regimens.

In a controlled postmarketing discontinuation study of panic disorder patients which compared the recommended taper schedule with a slower taper schedule, no difference was observed between the groups in the proportion of patients who tapered to zero dose; however, the slower schedule was associated with a reduction in symptoms associated with a withdrawal syndrome.

2.4 Dosage Recommendations in Geriatric Patients

In geriatric patients, the recommended starting oral dosage of XANAX is 0.25 mg, given 2 or 3 times daily. This may be gradually increased if needed and tolerated. Geriatric patients may be especially sensitive to the effects of benzodiazepines. If adverse reactions occur at the recommended starting dosage, the dosage may be reduced [see Use in Specific Populations (8.5), Clinical Pharmacology (12.3)].

2.5 Dosage Recommendations in Patients with Hepatic Impairment

In patients with hepatic impairment, the recommended starting oral dosage of XANAX is 0.25 mg, given 2 or 3 times daily. This may be gradually increased if needed and tolerated. If adverse reactions occur at the recommended starting dose, the dosage may be reduced [see Use in Specific Populations (8.6), Clinical Pharmacology (12.3)].

2.6 Dosage Modifications for Drug Interactions

XANAX should be reduced to half of the recommended dosage when a patient is started on ritonavir and XANAX together, or when ritonavir administered to a patient treated with XANAX. Increase the XANAX dosage to the target dose after 10 to 14 days of dosing ritonavir and XANAX together. It is not necessary to reduce XANAX dose in patients who have been taking ritonavir for more than 10 to 14 days.

XANAX is contraindicated with concomitant use of all strong CYP3A inhibitors, except ritonavir [see Contraindications (4), Warnings and Precautions (5.5)].

3 DOSAGE FORMS AND STRENGTHS

XANAX tablets are available as:

- 0.25 mg: white, oval, scored, imprinted “XANAX 0.25”
- 0.5 mg: peach, oval, scored, imprinted “XANAX 0.5”
- 1 mg: blue, oval, scored, imprinted “XANAX 1.0”
- 2 mg: white, oblong, multi-scored, imprinted “XANAX ” on one side and “2” on the reverse side

4 CONTRAINDICATIONS

XANAX is contraindicated in patients:

- with known hypersensitivity to alprazolam or other benzodiazepines. Angioedema has been reported [see Adverse Reactions (6.2)].
- taking strong cytochrome P450 3A (CYP3A) inhibitors (e.g., ketoconazole, itraconazole), except ritonavir [see Dosage and Administration (2.6), Warnings and Precautions (5.5), Drug Interactions (7.1)]

5 WARNINGS AND PRECAUTIONS

5.1 Risks from Concomitant Use with Opioids

Concomitant use of benzodiazepines, including XANAX, and opioids may result in profound sedation, respiratory depression, coma, and death. Because of these risks, reserve concomitant prescribing of these drugs in patients for whom alternative treatment options are inadequate.

Observational studies have demonstrated that concomitant use of opioid analgesics and benzodiazepines increases the risk of drug-related mortality compared to use of opioids alone. If a decision is made to prescribe XANAX concomitantly with opioids, prescribe the lowest effective dosages and minimum durations of concomitant use, and follow patients closely for signs and symptoms of respiratory depression and sedation. In patients already receiving an opioid analgesic, prescribe a lower initial dose of XANAX than indicated in the absence of an opioid and titrate based on clinical response. If an opioid is initiated in a patient already taking XANAX, prescribe a lower initial dose of the opioid and titrate based upon clinical response.

Advise both patients and caregivers about the risks of respiratory depression and sedation when XANAX is used with opioids. Advise patients not to drive or operate heavy machinery until the effects of concomitant use with the opioid have been determined [see Drug Interactions (7.1)].

5.2 Abuse, Misuse, and Addiction

The use of benzodiazepines, including XANAX, exposes users to the risks of abuse, misuse, and addiction, which can lead to overdose or death. Abuse and misuse of benzodiazepines often (but not always) involve the use of doses greater than the maximum recommended dosage and commonly involve concomitant use of other medications, alcohol, and/or illicit substances, which is associated with an increased frequency of serious adverse outcomes, including respiratory depression, overdose, or death [see Drug Abuse and Dependence (9.2)].

Before prescribing XANAX and throughout treatment, assess each patient’s risk for abuse, misuse, and addiction (e.g., using a standardized screening tool). Use of XANAX, particularly in patients at elevated risk, necessitates counseling about the risks and proper use of XANAX along with monitoring for signs and symptoms of abuse, misuse, and addiction. Prescribe the lowest effective dosage; avoid or minimize concomitant use of CNS depressants and other substances associated with abuse, misuse, and addiction (e.g., opioid analgesics, stimulants); and advise patients on the proper disposal of unused drug. If a substance use disorder is suspected, evaluate the patient and institute (or refer them for) early treatment, as appropriate.

5.3 Dependence and Withdrawal Reactions

To reduce the risk of withdrawal reactions, use a gradual taper to discontinue XANAX or reduce the dosage (a patient-specific plan should be used to taper the dose) [see Dosage and Administration (2.3)].

Patients at an increased risk of withdrawal adverse reactions after benzodiazepine discontinuation or rapid dosage reduction include those who take higher dosages, and those who have had longer durations of use.

Acute Withdrawal Reactions

The continued use of benzodiazepines, including XANAX, may lead to clinically significant physical dependence. Abrupt discontinuation or rapid dosage reduction of XANAX after continued use, or administration of flumazenil (a benzodiazepine antagonist) may precipitate acute withdrawal reactions, which can be life-threatening (e.g., seizures) [see Drug Abuse and Dependence (9.3)].

Protracted Withdrawal Syndrome

In some cases, benzodiazepine users have developed a protracted withdrawal syndrome with withdrawal symptoms lasting weeks to more than 12 months [see Drug Abuse and Dependence (9.3)].

Certain adverse clinical events, some life-threatening, are a direct consequence of physical dependence to XANAX. These include a spectrum of withdrawal symptoms; the most important is seizure [see Drug Abuse and Dependence (9.3)]. Even after relatively short-term use at doses of ≤4 mg/day, there is some risk of dependence. Spontaneous reporting system data suggest that the risk of dependence and its severity appear to be greater in patients treated with doses greater than 4 mg/day and for long periods (more than 12 weeks). However, in a controlled postmarketing discontinuation study of panic disorder patients who received XANAX, the duration of treatment (3 months compared to 6 months) had no effect on the ability of patients to taper to zero dose. In contrast, patients treated with doses of XANAX greater than 4 mg/day had more difficulty tapering to zero dose than those treated with less than 4 mg/day.

In a controlled clinical trial in which 63 patients were randomized to XANAX and where withdrawal symptoms were specifically sought, the following were identified as symptoms of withdrawal: heightened sensory perception, impaired concentration, dysosmia, clouded sensorium, paresthesias, muscle cramps, muscle twitch, diarrhea, blurred vision, appetite decrease, and weight loss. Other symptoms, such as anxiety and insomnia, were frequently seen during discontinuation, but it could not be determined if they were due to return of illness, rebound, or withdrawal.

Interdose Symptoms

Early morning anxiety and emergence of anxiety symptoms between doses of XANAX have been reported in patients with panic disorder taking prescribed maintenance doses. These symptoms may reflect the development of tolerance or a time interval between doses which is longer than the duration of clinical action of the administered dose. In either case, it is presumed that the prescribed dose is not sufficient to maintain plasma levels above those needed to prevent relapse, rebound, or withdrawal symptoms over the entire course of the interdosing interval.

5.4 Effects on Driving and Operating Machinery

Because of its CNS depressant effects, patients receiving XANAX should be cautioned against engaging in hazardous occupations or activities requiring complete mental alertness such as operating machinery or driving a motor vehicle. For the same reason, patients should be cautioned about the concomitant use of alcohol and other CNS depressant drugs during treatment with XANAX [see Drug Interactions (7.1)].

5.5 Interaction with Drugs that Inhibit Metabolism via Cytochrome P450 3A

The initial step in alprazolam metabolism is hydroxylation catalyzed by cytochrome P450 3A (CYP3A). Drugs that inhibit this metabolic pathway may have a profound effect on the clearance of alprazolam.

Strong CYP3A Inhibitors

XANAX is contraindicated in patients receiving strong inhibitors of CYP3A (such as azole antifungal agents), except ritonavir [see Contraindications (4)]. Ketoconazole and itraconazole have been shown in vivo to increase plasma alprazolam concentrations 3.98 fold and 2.70 fold, respectively.

Dosage adjustment is necessary when XANAX and ritonavir are initiated concomitantly or when ritonavir is added to a stable dosage of XANAX [see Dosage and Administration (2.6), Drug Interactions (7.1)].

Drugs demonstrated to be CYP3A inhibitors on the basis of clinical studies involving alprazolam: nefazodone, fluvoxamine, and cimetidine [see Drug Interaction (7.1), Clinical Pharmacology (12.3)]. Use caution and consider dose reduction of XANAX, as appropriate, during co-administration with these drugs.

5.6 Patients with Depression

Benzodiazepines may worsen depression. Panic disorder has been associated with primary and secondary major depressive disorders and increased reports of suicide among untreated patients. Consequently, appropriate precautions (e.g., limiting the total prescription size and increased monitoring for suicidal ideation) should be considered in patients with depression.

5.7 Mania

Episodes of hypomania and mania have been reported in association with the use of XANAX in patients with depression [see Adverse Reactions (6.2)].

5.8 Neonatal Sedation and Withdrawal Syndrome

Use of XANAX late in pregnancy can result in sedation (respiratory depression, lethargy, hypotonia) and/or withdrawal symptoms (hyperreflexia, irritability, restlessness, tremors, inconsolable crying, and feeding difficulties) in the neonate [see Use in Specific Populations (8.1)]. Monitor neonates exposed to XANAX during pregnancy or labor for signs of sedation and monitor neonates exposed to XANAX during pregnancy for signs of withdrawal; manage these neonates accordingly.

5.9 Risk in Patients with Impaired Respiratory Function

There have been reports of death in patients with severe pulmonary disease shortly after the initiation of treatment with XANAX. Closely monitor patients with impaired respiratory function. If signs and symptoms of respiratory depression, hypoventilation, or apnea occur, discontinue XANAX.

6 ADVERSE REACTIONS

The following clinically significant adverse reactions are described elsewhere in the labeling:

- Risks from Concomitant Use with Opioids [see Warnings and Precautions (5.1)]
- Abuse, Misuse, and Addiction [see Warnings and Precautions (5.2)]
- Dependence and Withdrawal Reactions [see Warnings and Precautions (5.3)]
- Effects on Driving and Operating Machinery [see Warnings and Precautions (5.4)]
- Patients with Depression [see Warnings and Precautions (5.6)]
- Neonatal Sedation and Withdrawal Syndrome [see Warnings and Precautions (5.8)]
- Risks in Patients with Impaired Respiratory Function [see Warnings and Precautions (5.9)]

6.1 Clinical Trials Experience

Because clinical trials are conducted under widely varying conditions, adverse reaction rates observed in the clinical trials of a drug cannot be directly compared to rates in the clinical trials of another drug and may not reflect the rates observed in practice.

The data in the two tables below are estimates of adverse reaction incidence among adult patients who participated in:

- 4-week placebo‑controlled clinical studies with XANAX dosages up to 4 mg per day for the acute treatment of generalized anxiety disorder (Table 1)
- Short‑term (up to 10 weeks) placebo‑controlled clinical studies with XANAX dosages up to 10 mg per day for panic disorder, with or without agoraphobia (Table 2).

Table 1: Adverse Reactions Occurring in ≥1% in XANAX-treated Patients and Greater than Placebo-treated Patients in Placebo-Controlled Trials for Generalized Anxiety
 | XANAX n=565 | Placebo n=505
Nervous system disorders; Drowsiness; Light-headedness; Dizziness; Akathisia | 41%; 21%; 2%; 2% | 22%; 19%; 1%; 1%
Gastrointestinal disorders; Dry mouth; Increased salivation | 15%; 4% | 13%; 2%
Cardiovascular disorders; Hypotension | 5% | 2%
Skin and subcutaneous tissue disorders; Dermatitis/allergy | 4% | 3%

In addition to the adverse reactions (i.e., greater than 1%) enumerated in the table above for patients with generalized anxiety disorder, the following adverse reactions have been reported in association with the use of benzodiazepines: dystonia, irritability, concentration difficulties, anorexia, transient amnesia or memory impairment, loss of coordination, fatigue, seizures, sedation, slurred speech, jaundice, musculoskeletal weakness, pruritus, diplopia, dysarthria, changes in libido, menstrual irregularities, incontinence and urinary retention.

Table 2: Adverse Reactions Occurring in ≥1% in XANAX-treated Patients and Greater than Placebo-treated Patients in Placebo-Controlled Trials (Up to 10 Weeks) for Panic Disorder
 | XANAX n=1388 | Placebo n=1231
Drowsiness; Fatigue and Tiredness; Impaired Coordination; Irritability; Memory Impairment; Cognitive Disorder; Decreased Libido; Dysarthria; Confusional state; Increased libido; Change in libido (not specified); Disinhibition; Talkativeness; Derealization | 77%; 49%; 40%; 33%; 33%; 29%; 14%; 23%; 10%; 8%; 7%; 3%; 2%; 2% | 43%; 42%; 18%; 30%; 22%; 21%; 8%; 6%; 8%; 4%; 6%; 2%; 1%; 1%
Gastrointestinal disorders; Constipation; Increased salivation | 26%; 6% | 15%; 4%
Skin and subcutaneous tissue disorders; Rash | 11% | 8%
Other; Increased appetite; Decreased appetite; Weight gain; Weight loss; Micturition difficulties; Menstrual disorders; Sexual dysfunction; Incontinence | 33%; 28%; 27%; 23%; 12%; 11%; 7%; 2% | 23%; 24%; 18%; 17%; 9%; 9%; 4%; 1%

In addition to the reactions (i.e., greater than 1%) enumerated in the table above for patients with panic disorder, the following adverse reactions have been reported in association with the use of XANAX: seizures, hallucinations, depersonalization, taste alterations, diplopia, elevated bilirubin, elevated hepatic enzymes, and jaundice.

Adverse Reactions Reported as Reasons for Discontinuation in Treatment of Panic Disorder in Placebo–Controlled Trials

In a larger database comprised of both controlled and uncontrolled studies in which 641 patients received XANAX, discontinuation‑emergent symptoms which occurred at a rate of over 5% in patients treated with XANAX and at a greater rate than the placebo‑treated group are shown in Table 3.

Table 3: Discontinuation-Emergent Symptom Incidence Reported in ≥5% of XANAX-treated Patients and > Placebo-treated Patients
 | XANAX-treated Patients; n=641
Nervous system disorders; Insomnia; Light-headedness; Abnormal involuntary movement; Headache; Muscular twitching; Impaired coordination; Muscle tone disorders; Weakness | 29.5%; 19.3%; 17.3%; 17.0%; 6.9%; 6.6%; 5.9%; 5.8%
Psychiatric disorders; Anxiety; Fatigue and Tiredness; Irritability; Cognitive disorder; Memory impairment; Depression; Confusional state | 19.2%; 18.4%; 10.5%; 10.3%; 5.5%; 5.1%; 5.0%
Gastrointestinal disorders; Nausea/Vomiting; Diarrhea; Decreased salivation | 16.5%; 13.6%; 10.6%
Metabolism and nutrition disorders; Weight loss; Decreased appetite | 13.3%; 12.8%
Dermatological disorders; Sweating | 14.4%
Cardiovascular disorders; Tachycardia | 12.2%
Special Senses; Blurred vision | 10.0%
n=number of patients.

There have also been reports of withdrawal seizures upon rapid decrease or abrupt discontinuation of XANAX [see Warning and Precautions (5.2) and Drug Abuse and Dependence (9.3)].

Paradoxical reactions such as stimulation, increased muscle spasticity, sleep disturbances, hallucinations, and other adverse behavioral effects such as agitation, rage, irritability, and aggressive or hostile behavior have been reported rarely. In many of the spontaneous case reports of adverse behavioral effects, patients were receiving other CNS drugs concomitantly and/or were described as having underlying psychiatric conditions. Should any of the above events occur, alprazolam should be discontinued. Isolated published reports involving small numbers of patients have suggested that patients who have borderline personality disorder, a prior history of violent or aggressive behavior, or alcohol or substance abuse may be at risk for such events. Instances of irritability, hostility, and intrusive thoughts have been reported during discontinuation of alprazolam in patients with posttraumatic stress disorder.

6.2 Postmarketing Experience

The following adverse reactions have been identified during postapproval use of XANAX. Because these reactions are reported voluntarily from a population of uncertain size, it is not always possible to reliably estimate their frequency or establish a causal relationship to drug exposure.

Endocrine disorders: Hyperprolactinemia
General disorders and administration site conditions: Edema peripheral
Hepatobiliary disorders: Hepatitis, hepatic failure
Investigations: Liver enzyme elevations
Psychiatric disorders: Hypomania, mania
Reproductive system and breast disorders: Gynecomastia, galactorrhea
Skin and subcutaneous tissue disorders: Photosensitivity reaction, angioedema, Stevens-Johnson syndrome

7 DRUG INTERACTIONS

7.1 Drugs Having Clinically Important Interactions with XANAX

Table 4 includes clinically significant drug interactions with XANAX [see Clinical Pharmacology (12.3)].

Table 4: Clinically Significant Drug Interactions with XANAX
Opioids
Clinical implication | The concomitant use of benzodiazepines and opioids increases the risk of respiratory depression because of actions at different receptor sites in the CNS that control respiration. Benzodiazepines interact at gamma-aminobutyric acid (GABAA) sites and opioids interact primarily at mu receptors. When benzodiazepines and opioids are combined, the potential for benzodiazepines to significantly worsen opioid‑related respiratory depression exists.
Prevention or management | Limit dosage and duration of concomitant use of XANAX and opioids, and monitor patients closely for respiratory depression and sedation [see Warnings and Precautions (5.1)].
Examples | Morphine, buprenorphine, hydromorphone, oxymorphone, oxycodone, fentanyl, methadone, alfentanil, butorphanol, codeine, dihydrocodeine, meperidine, pentazocine, remifentanil, sufentanil, tapentadol, tramadol.
CNS Depressants
Clinical implication | The benzodiazepines, including alprazolam, produce additive CNS depressant effects when coadministered with other CNS depressants.
Prevention or management | Limit dosage and duration of XANAX during concomitant use with CNS depressants [see Warnings and Precautions (5.3)].
Examples | Psychotropic medications, anticonvulsants, antihistaminics, ethanol, and other drugs which themselves produce CNS depression.
Strong Inhibitors of CYP3A (except ritonavir)
Clinical implication | Concomitant use of XANAX with strong CYP3A inhibitors has a profound effect on the clearance of alprazolam, resulting in increased concentrations of alprazolam and increased risk of adverse reactions [see Clinical Pharmacology (12.3)].
Prevention or management | Concomitant use of XANAX with a strong CYP3A4 inhibitor (except ritonavir) is contraindicated [see Contraindications (4), Warnings and Precautions (5.5)].
Examples | Ketoconazole, itraconazole, clarithromycin
Moderate or Weak Inhibitors of CYP3A
Clinical implication | Concomitant use of XANAX with CYP3A inhibitors may increase the concentrations of XANAX, resulting in increased risk of adverse reactions of alprazolam [see Clinical Pharmacology (12.3)].
Prevention or management | Avoid use and consider appropriate dose reduction when XANAX is coadministered with a moderate or weak CYP3A inhibitor [see Warnings and Precautions (5.5)].
Examples | Nefazodone, fluvoxamine, cimetidine, erythromycin
CYP3A Inducers
Clinical implication | Concomitant use of CYP3A inducers can increase alprazolam metabolism and therefore can decease plasma levels of alprazolam [see Clinical Pharmacology (12.3)].
Prevention or management | Caution is recommended during coadministration with XANAX.
Examples | Carbamazepine, phenytoin
Ritonavir
Clinical implication | Interactions involving ritonavir and alprazolam are complex and time dependent. Short term administration of ritonavir increased alprazolam exposure due to CYP3A4 inhibition. Following long term treatment of ritonavir (>10 to 14 days), CYP3A4 induction offsets this inhibition.; Alprazolam exposure was not meaningfully affected in the presence of ritonavir.
Prevention or management | Reduce XANAX dosage when ritonavir and XANAX are initiated concomitantly, or when ritonavir is added to a regimen where XANAX is stabilized.; Increase XANAX dosage to the target dosage after 10 to 14 days of dosing ritonavir and XANAX concomitantly. No dosage adjustment of XANAX is necessary in patients receiving ritonavir for more than 10 to14 days [see Dosage and Administration (2.6)].; Concomitant use of XANAX with a strong CYP3A inhibitor, except ritonavir, is contraindicated [see Contraindications (4), Warnings and Precautions (5.5)].
Digoxin
Clinical implication | Increased digoxin concentrations have been reported when alprazolam was given, especially in geriatric patients (>65 years of age).
Prevention or management | In patients on digoxin therapy, measure serum digoxin concentrations before initiating XANAX. Continue monitoring digoxin serum concentration and toxicity frequently. Reduce the digoxin dose if necessary.

7.2 Drug/Laboratory Test Interactions

Although interactions between benzodiazepines and commonly employed clinical laboratory tests have occasionally been reported, there is no consistent pattern for a specific drug or specific test.

8 USE IN SPECIFIC POPULATIONS

8.1 Pregnancy

Pregnancy Exposure Registry

There is a pregnancy exposure registry that monitors pregnancy outcomes in women exposed to psychiatric medications, including XANAX, during pregnancy. Healthcare providers are encouraged to register patients by calling the National Pregnancy Registry for Psychiatric Medications at 1-866-961-2388 or visiting online at https://womensmentalhealth.org/research/pregnancyregistry/.

Risk Summary

Neonates born to mothers using benzodiazepines late in pregnancy have been reported to experience symptoms of sedation and/or neonatal withdrawal [see Warnings and Precautions (5.8) and Clinical Considerations)]. Available data from published observational studies of pregnant women exposed to benzodiazepines do not report a clear association with benzodiazepines and major birth defects (see Data).

The background risk of major birth defects and miscarriage for the indicated population is unknown. All pregnancies have a background risk of birth defect, loss, or other adverse outcomes. In the U.S. general population, the estimated risk of major birth defects and of miscarriage in clinically recognized pregnancies is 2% to 4% and 15% to 20%, respectively.

Clinical Considerations

Fetal/Neonatal adverse reactions

Benzodiazepines cross the placenta and may produce respiratory depression, hypotonia, and sedation in neonates. Monitor neonates exposed to XANAX during pregnancy or labor for signs of sedation, respiratory depression, hypotonia, and feeding problems. Monitor neonates exposed to XANAX during pregnancy for signs of withdrawal. Manage these neonates accordingly [see Warnings and Precautions (5.8)].

Data

Human Data

Published data from observational studies on the use of benzodiazepines during pregnancy do not report a clear association with benzodiazepines and major birth defects. Although early studies reported an increased risk of congenital malformations with diazepam and chlordiazepoxide, there was no consistent pattern noted. In addition, the majority of recent case-control and cohort studies of benzodiazepine use during pregnancy, which were adjusted for confounding exposures to alcohol, tobacco, and other medications, have not confirmed these findings.

8.2 Lactation

Risk Summary

Limited data from published literature reports the presence of alprazolam in human breast milk. There are reports of sedation, poor feeding and poor weight gain in infants exposed to benzodiazepines through breast milk. The effects of alprazolam on lactation are unknown.

Because of the potential for serious adverse reactions, including sedation and withdrawal symptoms in breastfed infants, advise patients that breastfeeding is not recommended during treatment with XANAX.

8.4 Pediatric Use

Safety and effectiveness of XANAX have not been established in pediatric patients.

8.5 Geriatric Use

XANAX-treated geriatric patients had higher plasma concentrations of alprazolam (due to reduced clearance) compared to younger adult patients receiving the same doses. Therefore, dosage reduction of XANAX is recommended in geriatric patients [see Dosage and Administration (2.4) and Clinical Pharmacology (12.3)].

8.6 Hepatic Impairment

Patients with alcoholic liver disease exhibit a longer elimination half-life (19.7 hours), compared to healthy subjects (11.4 hours). This may be caused by decreased clearance of alprazolam in patients with alcoholic liver disease. Dosage reduction of XANAX is recommended in patients with hepatic impairment [see Dosage and Administration (2.4), Clinical Pharmacology (12.3)].

9 DRUG ABUSE AND DEPENDENCE

9.1 Controlled Substance

XANAX contains alprazolam, which is a Schedule IV controlled substance.

9.2 Abuse

XANAX is a benzodiazepine and a CNS depressant with a potential for abuse and addiction. Abuse is the intentional, non-therapeutic use of a drug, even once, for its desirable psychological or physiological effects. Misuse is the intentional use, for therapeutic purposes, of a drug by an individual in a way other than prescribed by a health care provider or for whom it was not prescribed. Drug addiction is a cluster of behavioral, cognitive, and physiological phenomena that may include a strong desire to take the drug, difficulties in controlling drug use (e.g., continuing drug use despite harmful consequences, giving a higher priority to drug use than other activities and obligations), and possible tolerance or physical dependence. Even taking benzodiazepines as prescribed may put patients at risk for abuse and misuse of their medication. Abuse and misuse of benzodiazepines may lead to addiction.

Abuse and misuse of benzodiazepines often (but not always) involve the use of doses greater than the maximum recommended dosage and commonly involve concomitant use of other medications, alcohol, and/or illicit substances, which is associated with an increased frequency of serious adverse outcomes, including respiratory depression, overdose, or death. Benzodiazepines are often sought by individuals who abuse drugs and other substances, and by individuals with addictive disorders [see Warnings and Precautions (5.2)].

The following adverse reactions have occurred with benzodiazepine abuse and/or misuse: abdominal pain, amnesia, anorexia, anxiety, aggression, ataxia, blurred vision, confusion, depression, disinhibition, disorientation, dizziness, euphoria, impaired concentration and memory, indigestion, irritability, muscle pain, slurred speech, tremors, and vertigo.

The following severe adverse reactions have occurred with benzodiazepine abuse and/or misuse: delirium, paranoia, suicidal ideation and behavior, seizures, coma, breathing difficulty, and death. Death is more often associated with polysubstance use (especially benzodiazepines with other CNS depressants such as opioids and alcohol).

9.3 Dependence

XANAX may produce physical dependence from continued therapy. Physical dependence is a state that develops as a result of physiological adaptation in response to repeated drug use, manifested by withdrawal signs and symptoms after abrupt discontinuation or a significant dose reduction of a drug. Abrupt discontinuation or rapid dosage reduction of benzodiazepines or administration of flumazenil, a benzodiazepine antagonist, may precipitate acute withdrawal reactions, including seizures, which can be life-threatening. Patients at an increased risk of withdrawal adverse reactions after benzodiazepine discontinuation or rapid dosage reduction include those who take higher dosages (i.e., higher and/or more frequent doses) and those who have had longer durations of use [see Warnings and Precautions (5.3)].

To reduce the risk of withdrawal reactions, use a gradual taper to discontinue XANAX or reduce the dosage [see Dosage and Administration (2.3), Warnings and Precautions (5.3)].

Acute Withdrawal Signs and Symptoms

Acute withdrawal signs and symptoms associated with benzodiazepines have included abnormal involuntary movements, anxiety, blurred vision, depersonalization, depression, derealization, dizziness, fatigue, gastrointestinal adverse reactions (e.g., nausea, vomiting, diarrhea, weight loss, decreased appetite), headache, hyperacusis, hypertension, irritability, insomnia, memory impairment, muscle pain and stiffness, panic attacks, photophobia, restlessness, tachycardia, and tremor. More severe acute withdrawal signs and symptoms, including life-threatening reactions, have included catatonia, convulsions, delirium tremens, depression, hallucinations, mania, psychosis, seizures, and suicidality.

Protracted Withdrawal Syndrome

Protracted withdrawal syndrome associated with benzodiazepines is characterized by anxiety, cognitive impairment, depression, insomnia, formication, motor symptoms (e.g., weakness, tremor, muscle twitches), paresthesia, and tinnitus that persists beyond 4 to 6 weeks after initial benzodiazepine withdrawal. Protracted withdrawal symptoms may last weeks to more than 12 months. As a result, there may be difficulty in differentiating withdrawal symptoms from potential re-emergence or continuation of symptoms for which the benzodiazepine was being used.

Tolerance

Tolerance to XANAX may develop from continued therapy. Tolerance is a physiological state characterized by a reduced response to a drug after repeated administration (i.e., a higher dose of a drug is required to produce the same effect that was once obtained at a lower dose). Tolerance to the therapeutic effect of XANAX may develop; however, little tolerance develops to the amnestic reactions and other cognitive impairments caused by benzodiazepines.

10 OVERDOSAGE

Overdosage of benzodiazepines is characterized by central nervous system depression ranging from drowsiness to coma. In mild to moderate cases, symptoms can include drowsiness, confusion, dysarthria, lethargy, hypnotic state, diminished reflexes, ataxia, and hypotonia. Rarely, paradoxical or disinhibitory reactions (including agitation, irritability, impulsivity, violent behavior, confusion, restlessness, excitement, and talkativeness) may occur. In severe overdosage cases, patients may develop respiratory depression and coma. Overdosage of benzodiazepines in combination with other CNS depressants (including alcohol and opioids) may be fatal [see Warnings and Precautions (5.2)]. Markedly abnormal (lowered or elevated) blood pressure, heart rate, or respiratory rate raise the concern that additional drugs and/or alcohol are involved in the overdosage.

In managing benzodiazepine overdosage, employ general supportive measures, including intravenous fluids and airway management. Flumazenil, a specific benzodiazepine receptor antagonist indicated for the complete or partial reversal of the sedative effects of benzodiazepines in the management of benzodiazepine overdosage, can lead to withdrawal and adverse reactions, including seizures, particularly in the context of mixed overdosage with drugs that increase seizure risk (e.g., tricyclic and tetracyclic antidepressants) and in patients with long-term benzodiazepine use and physical dependency. The risk of withdrawal seizures with flumazenil use may be increased in patients with epilepsy. Flumazenil is contraindicated in patients who have received a benzodiazepine for control of a potentially life-threatening condition (e.g., status epilepticus). If the decision is made to use flumazenil, it should be used as an adjunct to, not as a substitute for, supportive management of benzodiazepine overdosage. See the flumazenil injection Prescribing Information.

Consider contacting the Poison Help Line (1-800-222-1222), or a medical toxicologist for additional overdosage management recommendations.

11 DESCRIPTION

XANAX contains alprazolam which is a triazolo analog of the 1,4 benzodiazepine class of central nervous system-active compounds.

The chemical name of alprazolam is 8-Chloro-1-methyl-6-phenyl-4H-s-triazolo [4,3-α] [1,4] benzodiazepine.

The structural formula is:

Alprazolam is a white crystalline powder, which is soluble in methanol or ethanol but which has no appreciable solubility in water at physiological pH.

Each XANAX tablet, for oral administration, contains 0.25 mg, 0.5 mg, 1 mg, or 2 mg of alprazolam.

Inactive ingredients: cellulose, corn starch, docusate sodium, lactose, magnesium stearate, silicon dioxide and sodium benzoate. In addition, the 0.5 mg tablet contains FD&C Yellow No. 6 and the 1 mg tablet contains FD&C Blue No. 2.

12 CLINICAL PHARMACOLOGY

12.1 Mechanism of Action

Alprazolam is a 1,4 benzodiazepine. Alprazolam exerts its effect for the acute treatment of generalized anxiety disorder and panic disorder through binding to the benzodiazepine site of gamma‑aminobutyric acid-A (GABAA) receptors in the brain and enhances GABA-mediated synaptic inhibition.

12.3 Pharmacokinetics

Plasma levels of alprazolam increase proportionally to the dose over the range of 0.5 to 3.0 mg.

Absorption

Following oral administration, peak plasma concentration of alprazolam (Cmax) occurs in 1 to 2 hours post dose.

Distribution

Alprazolam is 80% bound to human serum protein, and albumin accounts for the majority of the binding.

Elimination

The mean plasma elimination half-life (T1/2) of alprazolam is approximately 11.2 hours (range: 6.3 to 26.9 hours) in healthy adults.

Metabolism

Alprazolam is extensively metabolized in humans, primarily by cytochrome P450 3A4 (CYP3A4), to 2 major active metabolites in the plasma: 4‑hydroxyalprazolam and α‑hydroxyalprazolam. The plasma circulation levels of the two active metabolites are less than 4% of the parent. The reported relative potencies in benzodiazepine receptor binding experiments and in animal models of induced seizure inhibition are 0.20 and 0.66, respectively, for 4‑hydroxyalprazolam and α‑hydroxyalprazolam. The low concentrations and low potencies of 4-hydroxyalprazolam and α-hydroxyalprazolam indicate that they unlikely contribute much to the effects of alprazolam. A benzophenone derived from alprazolam is also found in humans. Their half-lives appear to be similar to that of alprazolam.

Excretion

Alprazolam and its metabolites are excreted primarily in the urine.

Specific Populations

Geriatric Patients

The mean T1/2 of alprazolam was 16.3 hours (range: 9.0 to 26.9 hours) in healthy elderly subjects compared to 11.0 hours (range: 6.3 to -15.8 hours, n=16) in healthy younger adult subjects.

Obese Patients

The mean T1/2 of alprazolam was 21.8 hours (range: 9.9 to 40.4 hours) in a group of obese subjects.

Patients with Hepatic Impairment

The mean T1/2 of alprazolam was 19.7 hours (range: 5.8 to 65.3 hours) in patients with alcoholic liver disease.

Racial or Ethnic Groups

Maximal concentrations and T1/2 of alprazolam are approximately 15% and 25% higher in Asians compared to Caucasians.

Smoking

Alprazolam concentrations may be reduced by up to 50% in smokers compared to non‑smokers.

Drug Interaction Studies

In Vivo Studies

Most of the interactions that have been documented with alprazolam are with drugs that modulate CYP3A4 activity.

Compounds that are inhibitors or inducers of CYP3A would be expected to increase or decrease plasma alprazolam concentrations, respectively. Drug products that have been studied in vivo, along with their effect on increasing alprazolam AUC, are as follows: ketoconazole, 3.98 fold; itraconazole, 2.66 fold; nefazodone, 1.98 fold; fluvoxamine, 1.96 fold; and erythromycin, 1.61 fold [see Contraindications (4), Warnings and Precautions (5.5), Drug Interactions (7.2)]. Other studied drugs include:

Cimetidine: Coadministration of cimetidine increased the maximum plasma concentration of alprazolam by 82%, decreased clearance by 42%, and increased T1/2 by 16%.

Fluoxetine: Coadministration of fluoxetine with alprazolam increased the maximum plasma concentration of alprazolam by 46%, decreased clearance by 21%, increased T1/2 by 17%, and decreased measured psychomotor performance.

Oral Contraceptives: Coadministration of oral contraceptives increased the maximum plasma concentration of alprazolam by 18%, decreased clearance by 22%, and increased T1/2 by 29%.

Carbamazepine: The oral clearance of alprazolam (given in a 0.8 mg single dose) was increased from 0.90±0.21 mL/min/kg to 2.13±0.54 mL/min/kg and the elimination T1/2 was shortened (from 17.1±4.9 to 7.7±1.7 hour) following administration of 300 mg per day carbamazepine for 10 days [see Drug Interactions (7.2)]. However, the carbamazepine dose used in this study was fairly low compared to the recommended doses (1000‑1200 mg per day); the effect at usual carbamazepine doses is unknown.

Ritonavir: Interactions involving HIV protease inhibitors (e.g., ritonavir) and alprazolam are complex and time dependent. Short-term low doses of ritonavir (4 doses of 200 mg) increased mean AUC of alprazolam by about 2.5-fold, and did not significantly affect Cmax of alprazolam. The elimination T1/2 was prolonged (30 hours versus 13 hours). However, upon extended exposure to ritonavir (500 mg, twice daily for 10 days), CYP3A induction offset this inhibition. Alprazolam AUC and Cmax was reduced by 12% and 16%, respectively, in the presence of ritonavir. The elimination T1/2 of alprazolam was not significantly changed [see Warnings and Precautions (5.5)].

Sertraline: A single dose of alprazolam 1 mg and steady state dose of sertraline (50 mg to 150 mg per day) did not reveal any clinically significant changes in the pharmacokinetics of alprazolam.

Imipramine and Desipramine: The steady state plasma concentrations of imipramine and desipramine have been reported to be increased an average of 31% and 20%, respectively, by the concomitant administration of XANAX in doses up to 4 mg per day.

Warfarin: Alprazolam did not affect the prothrombin or plasma warfarin levels in male volunteers administered sodium warfarin orally.

In Vitro Studies

Data from in vitro studies of alprazolam suggest a possible drug interaction of alprazolam with paroxetine.

The ability of alprazolam to induce human hepatic enzyme systems has not yet been determined.

13 NONCLINICAL TOXICOLOGY

13.1 Carcinogenesis, Mutagenesis, Impairment of Fertility

Carcinogenesis

No evidence of carcinogenic potential was observed in rats or mice administered alprazolam for 2 years at doses up to 30 and 10 mg/kg day respectively. These doses are 29 times and 4.8 times the maximum recommended human dose of 10 mg/day based on mg/m^2 body surface area, respectively.

Mutagenesis

Alprazolam was negative in the in vitro Ames bacterial reverse mutation assay and DNA Damage/Alkaline Elution Assay and in vivo rat micronucleus genetic toxicology assays.

Impairment of Fertility

Alprazolam produced no impairment of fertility in rats at doses up to 5 mg/kg per day, which is approximately 5 times the maximum recommended human dose of 10 mg per day based on mg/m^2 body surface area.

13.2 Animal Toxicology and/or Pharmacology

When rats were treated with alprazolam at oral doses of 3 mg, 10 mg, and 30 mg/kg day (3 to 29 times the maximum recommended human dose based on mg/m^2 body surface area) for 2 years, a tendency for a dose related increase in the number of cataracts was observed in females and a tendency for a dose related increase in corneal vascularization was observed in males. These lesions did not appear until after 11 months of treatment.

14 CLINICAL STUDIES

14.1 Generalized Anxiety Disorder

XANAX was compared to placebo in double‑blind clinical studies (doses up to 4 mg per day) in patients with a diagnosis of anxiety or anxiety with associated depressive symptomatology. XANAX was significantly better than placebo at each of the evaluation periods of these 4‑week studies as judged by the following psychometric instruments: Physician’s Global Impressions, Hamilton Anxiety Rating Scale, Target Symptoms, Patient’s Global Impressions, and Self-Rating Symptom Scale.

14.2 Panic Disorder

The effectiveness of XANAX in the treatment of panic disorder was studied in 3 short‑term, placebo‑controlled studies (up to 10 weeks) in patients with diagnoses closely corresponding to DSM-III-R criteria for panic disorder.

The average dose of XANAX was 5 mg to 6 mg per day in 2 of the studies, and the doses of XANAX were fixed at 2 mg and 6 mg per day in the third study. In all 3 studies, XANAX was superior to placebo on a variable defined as “the number of patients with zero panic attacks” (range, 37% to 83% met this criterion), as well as on a global improvement score. In 2 of the 3 studies, XANAX was superior to placebo on a variable defined as “change from baseline on the number of panic attacks per week” (range, 3.3 to 5.2), and also on a phobia rating scale. A subgroup of patients who improved on XANAX during short-term treatment in 1 of these trials was continued on an open basis up to 8 months, without apparent loss of benefit.

16 HOW SUPPLIED/STORAGE AND HANDLING

XANAX is supplied in the following strengths and package configurations:

XANAX Tablets
Package Configuration | Tablet Strength (mg) | NDC | Print
Bottles of 100; Bottles of 500 | 0.25 mg | NDC 58151-452-01; NDC 58151-452-05 | white, oval, scored, imprinted “XANAX 0.25”
Bottles of 100; Bottles of 500 | 0.5 mg | NDC 58151-453-01; NDC 58151-453-05 | peach, oval, scored, imprinted “XANAX 0.5”
Bottles of 100; Bottles of 500 | 1 mg | NDC 58151-454-01; NDC 58151-454-05 | blue, oval, scored, imprinted “XANAX 1.0”
Bottles of 100 | 2 mg | NDC 58151-455-01 | white, oblong, multi-scored, imprinted “XANAX” on one side and “2” on the reverse side

Store at controlled room temperature 20° to 25°C (68° to 77°F) [see USP Controlled Room Temperature].

17 PATIENT COUNSELING INFORMATION

Advise the patient to read the FDA‑approved patient labeling (Medication Guide).

Risks from Concomitant Use with Opioids

Advise both patients and caregivers about the risks of potentially fatal respiratory depression and sedation when XANAX is used with opioids and not to use such drugs concomitantly unless supervised by a healthcare provider. Advise patients not to drive or operate heavy machinery until the effects of concomitant use with the opioid have been determined [see Warnings and Precautions (5.1), Drug Interactions (7.1)].

Abuse, Misuse, and Addiction

Inform patients that the use of XANAX, even at recommended dosages, exposes users to risks of abuse, misuse, and addiction, which can lead to overdose and death, especially when used in combination with other medications (e.g., opioid analgesics), alcohol, and/or illicit substances. Inform patients about the signs and symptoms of benzodiazepine abuse, misuse, and addiction; to seek medical help if they develop these signs and/or symptoms; and on the proper disposal of unused drug [see Warnings and Precautions (5.2), Drug Abuse and Dependence (9.2)].

Withdrawal Reactions

Inform patients that the continued use of XANAX may lead to clinically significant physical dependence and that abrupt discontinuation or rapid dosage reduction of XANAX may precipitate acute withdrawal reactions, which can be life-threatening. Inform patients that in some cases, patients taking benzodiazepines have developed a protracted withdrawal syndrome with withdrawal symptoms lasting weeks to more than 12 months. Instruct patients that discontinuation or dosage reduction of XANAX may require a slow taper [see Warnings and Precautions (5.3), Drug Abuse and Dependence (9.3)].

Effects on Driving and Operating Machinery

Advise patients not to drive a motor vehicle or operate heavy machinery while taking XANAX due to its CNS depressant effects. Also advise patients to avoid use of alcohol or other CNS depressants while taking XANAX [see Warnings and Precautions (5.3)].

Patients with Depression

Advise patients, their families, and caregivers to look for signs of suicidality or worsening depression, and to inform the patient’s healthcare provider immediately [see Warnings and Precautions (5.6)].

Concomitant Medications

Advise patients to inform their healthcare provider of all medicines they take, including prescription and nonprescription medications, vitamins and herbal supplements [see Drug Interactions (7)].

Pregnancy

Advise pregnant females that use of XANAX late in pregnancy can result in sedation (respiratory depression, lethargy, hypotonia) and/or withdrawal symptoms (hyperreflexia, irritability, restlessness, tremors, inconsolable crying, and feeding difficulties) in newborns [see Warnings and Precautions (5.8), Use in Specific Populations (8.1)]. Instruct patients to inform their healthcare provider if they are pregnant.

Advise patients that there is a pregnancy exposure registry that monitors pregnancy outcomes in women exposed to XANAX during pregnancy [see Use in Specific Populations (8.1)].

Lactation

Advise patients that breastfeeding is not recommended during treatment with XANAX [see Use in Specific Populations (8.2)].

Distributed by:
Viatris Specialty LLC
Morgantown, WV 26505 U.S.A.

© 2024 Viatris Inc.

UPJ:XNXT:R1mmh

MEDICATION GUIDE

XANAX (ZAN-aks)

(alprazolam) tablets, C-IV

What is the most important information I should know about XANAX?

- XANAX is a benzodiazepine medicine. Taking benzodiazepines with opioid medicines, alcohol, or other central nervous system (CNS) depressants (including street drugs) can cause severe drowsiness, breathing problems (respiratory depression), coma and death. Get emergency help right away if any of the following happens:
  - shallow or slowed breathing
  - breathing stops (which may lead to the heart stopping)
  - excessive sleepiness (sedation)
    Do not drive or operate heavy machinery until you know how taking XANAX with opioids affects you.
- Risk of abuse, misuse, and addiction. There is a risk of abuse, misuse, and addiction with benzodiazepines, including XANAX, which can lead to overdose and serious side effects including coma and death.
  - Serious side effects including coma and death have happened in people who have abused or misused benzodiazepines, including XANAX. These serious side effects may also include delirium, paranoia, suicidal thoughts or actions, seizures, and difficulty breathing. Call your healthcare provider or go to the nearest hospital emergency room right away if you get any of these serious side effects.
  - You can develop an addiction even if you take XANAX as prescribed by your healthcare provider.
  - Take XANAX exactly as your healthcare provider prescribed.
  - Do not share your XANAX with other people.
  - Keep XANAX in a safe place and away from children.
- Physical dependence and withdrawal reactions. XANAX can cause physical dependence and withdrawal reactions.
  - Do not suddenly stop taking XANAX. Stopping XANAX suddenly can cause serious and life-threatening side effects, including, unusual movements, responses, or expressions, seizures, sudden and severe mental or nervous system changes, depression, seeing or hearing things that others do not see or hear, an extreme increase in activity or talking, losing touch with reality, and suicidal thoughts or actions. Call your healthcare provider or go to the nearest hospital emergency room right away if you get any of these symptoms.
  - Some people who suddenly stop benzodiazepines, have symptoms that can last for several weeks to more than 12 months, including, anxiety, trouble remembering, learning, or concentrating, depression, problems sleeping, feeling like insects are crawling under your skin, weakness, shaking, muscle twitching, burning or prickling feeling in your hands, arms, legs or feet, and ringing in your ears.
  - Physical dependence is not the same as drug addiction. Your healthcare provider can tell you more about the differences between physical dependence and drug addiction.
- Do not take more XANAX than prescribed or take XANAX for longer than prescribed.

What is XANAX?

- XANAX is a prescription medicine used:
  - to treat anxiety disorders
  - for the short-term relief of the symptoms of anxiety
  - to treat panic disorder with or without a fear of places and situations that might cause panic, helplessness, or embarrassment (agoraphobia)
- XANAX is a federal controlled substance (C-IV) because it contains alprazolam that can be abused or lead to dependence. Keep XANAX in a safe place to prevent misuse and abuse. Selling or giving away XANAX may harm others, and is against the law. Tell your healthcare provider if you have abused or been dependent on alcohol, prescription medicines or street drugs.
- It is not known if XANAX is safe and effective in children.
- Elderly patients are especially susceptible to dose related adverse effects when taking XANAX.
- It is not known if XANAX is safe and effective when used to treat anxiety disorder for longer than 4 months.
- It is not known if XANAX is safe and effective when used to treat panic disorder for longer than 10 weeks.

Do not take XANAX if:

- you are allergic to alprazolam, other benzodiazepines, or any of the ingredients in XANAX. See the end of this Medication Guide for a complete list of ingredients in XANAX.
- you are taking antifungal medicines including ketoconazole and itraconazole

Before you take XANAX, tell your healthcare provider about all of your medical conditions, including if you:

- have or have had depression, mood problems, or suicidal thoughts or behavior
- have liver or kidney problems
- have lung disease or breathing problems
- are pregnant or plan to become pregnant.
  - Taking XANAX late in pregnancy may cause your baby to have symptoms of sedation (breathing problems, sluggishness, low muscle tone), and/or withdrawal symptoms (jitteriness, irritability, restlessness, shaking, excessive crying, feeding problems).
  - Tell your healthcare provider right away if you become pregnant or think you are pregnant during treatment with XANAX.
  - There is a pregnancy registry for women who take XANAX during pregnancy. The purpose of the registry is to collect information about the health of you and your baby. If you become pregnant during treatment with XANAX, talk to your healthcare provider about registering with the National Pregnancy Registry for Psychiatric Medications. You can register by calling 1-866-961-2388 or visiting https://womensmentalhealth.org/pregnancyregistry/.
- are breastfeeding or plan to breastfeed. XANAX passes into your breast milk.
  - Talk to your healthcare provider about the best way to feed your baby if you take XANAX.
  - Breastfeeding is not recommended during treatment with XANAX.

Tell your healthcare provider about all the medicines you take, including prescription and over-the-counter medicines, vitamins, and herbal supplements.

Taking XANAX with certain other medicines can cause side effects or affect how well XANAX or the other medicines work. Do not start or stop other medicines without talking to your healthcare provider.

How should I take XANAX?

- See “What is the most important information I should know about XANAX?”
- Take XANAX exactly as your healthcare provider tells you to take it. Your healthcare provider will tell you how much XANAX to take and when to take it.
- If you take too much XANAX, call your healthcare provider or go to the nearest hospital emergency room right away.

What are the possible side effects of XANAX?

XANAX may cause serious side effects, including:

- See “What is the most important information I should know about XANAX?”
- Seizures. Stopping XANAX can cause seizures and seizures that will not stop (status epilepticus).
- Mania. XANAX may cause an increase in activity and talking (hypomania and mania) in people who have depression.
  - XANAX can make you sleepy or dizzy and can slow your thinking and motor skills. Do not drive, operate heavy machinery, or do other dangerous activities until you know how XANAX affects you.
  - Do not drink alcohol or take other drugs that may make you sleepy or dizzy while taking XANAX without first talking to your healthcare provider. When taken with alcohol or drugs that cause sleepiness or dizziness, XANAX may make your sleepiness or dizziness much worse.

The most common side effects of XANAX include:

- problems with coordination
- hypotension
- trouble saying words clearly (dysarthria)
- changes in sex drive (libido)

These are not all the possible side effects of XANAX. Call your doctor for medical advice about side effects. You may report side effects to FDA at 1-800-FDA-1088.

How should I store XANAX?

- Store XANAX at room temperature between 68°F to 77°F (20°C to 25°C)
- Keep XANAX and all medicines out of the reach of children.

General information about the safe and effective use of XANAX.

- Medicines are sometimes prescribed for purposes other than those listed in a Medication Guide.
- Do not use XANAX for a condition for which it was not prescribed.
- Do not give XANAX to other people, even if they have the same symptoms that you have. It may harm them.
- You can ask your pharmacist or healthcare provider for information about XANAX that is written for health professionals.

What are the ingredients in XANAX?

Active ingredient: alprazolam

Inactive ingredients: Cellulose, corn starch, docusate sodium, lactose, magnesium stearate, silicon dioxide and sodium benzoate. In addition, the 0.5 mg tablet contains FD&C Yellow No. 6 and the 1 mg tablet contains FD&C Blue No. 2.

XANAX® is a registered trademark of UPJOHN US 2 LLC, a Viatris Company.

For more information, call Viatris at 1-877-446-3679 (1-877-4-INFO-RX).

Distributed by:

Viatris Specialty LLC

Morgantown, WV 26505 U.S.A.

© 2024 Viatris Inc.

UPJ:MG:XNXT:R1m

This Medication Guide has been approved by the U.S. Food and Drug Administration. Revised: 4/2024

PRINCIPAL DISPLAY PANEL – 0.25 mg

ALWAYS DISPENSE WITH MEDICATION GUIDE

NDC 58151-452-01

Xanax® CIV
alprazolam
tablets, USP

0.25 mg

100 Tablets

Rx only

Store at controlled room
temperature 20° to 25°C
(68° to 77°F)
[see USP Controlled
Room Temperature].

Protect from light.

Dispense in tight (USP),
light-resistant, child-resistant
containers.

DOSAGE AND USE:
See accompanying
prescribing information.
Each tablet contains
0.25 mg alprazolam.

Distributed by:
Viatris Specialty LLC
Morgantown, WV 26505 U.S.A.

© 2024 Viatris Inc.

Made in Ireland

RUPJ452A

PRINCIPAL DISPLAY PANEL – 0.5 mg

ALWAYS DISPENSE WITH MEDICATION GUIDE

NDC 58151-453-01

Xanax® CIV
alprazolam
tablets, USP

0.5 mg

100 Tablets

Rx only

Store at controlled room
temperature 20° to 25°C
(68° to 77°F)
[see USP Controlled
Room Temperature].

Protect from light.

Dispense in tight (USP),
light-resistant, child-resistant
containers.

DOSAGE AND USE:
See accompanying
prescribing information.
Each tablet contains
0.5 mg alprazolam.

Distributed by:
Viatris Specialty LLC
Morgantown, WV 26505 U.S.A.

© 2024 Viatris Inc.

Made in Ireland

RUPJ453A

PRINCIPAL DISPLAY PANEL – 1 mg

ALWAYS DISPENSE WITH MEDICATION GUIDE

NDC 58151-454-01

Xanax® CIV
alprazolam
tablets, USP

1 mg

100 Tablets

Rx only

Store at controlled room
temperature 20° to 25°C
(68° to 77°F)
[see USP Controlled
Room Temperature].

Protect from light.

Dispense in tight (USP),
light-resistant, child-resistant
containers.

DOSAGE AND USE:
See accompanying
prescribing information.
Each tablet contains
1 mg alprazolam.

Distributed by:
Viatris Specialty LLC
Morgantown, WV 26505 U.S.A.

© 2024 Viatris Inc.

Made in Ireland

RUPJ454A

PRINCIPAL DISPLAY PANEL – 2 mg

ALWAYS DISPENSE WITH MEDICATION GUIDE

NDC 58151-455-01

Xanax® CIV
alprazolam
tablets, USP

2 mg

100 Tablets

Rx only

Store at controlled room
temperature 20° to 25°C
(68° to 77°F)
[see USP Controlled
Room Temperature].

Protect from light.

Dispense in tight (USP),
light-resistant, child-resistant
containers.

DOSAGE AND USE:
See accompanying
prescribing information.
Each tablet contains
2 mg alprazolam.

Distributed by:
Viatris Specialty LLC
Morgantown, WV 26505 U.S.A.

© 2024 Viatris Inc.

Made in Ireland

RUPJ455A